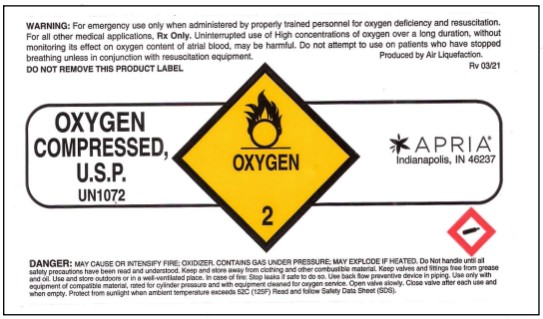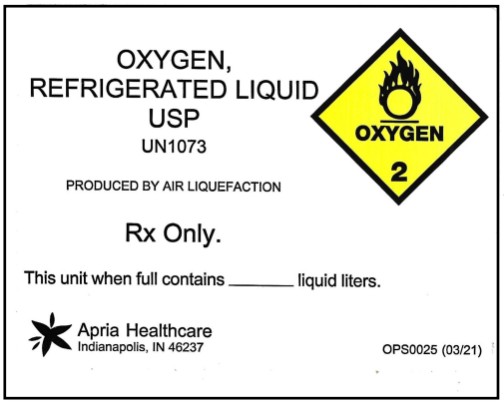 DRUG LABEL: Oxygen
NDC: 51319-072 | Form: GAS
Manufacturer: Apria Healthcare LLC
Category: prescription | Type: HUMAN PRESCRIPTION DRUG LABEL
Date: 20260304

ACTIVE INGREDIENTS: OXYGEN 0.995 mL/1 L

Oxygen

PRINCIPAL DISPLAY PANEL

OXYGEN
COMPRESSED,
U.S.P.
UN 1072

PRINCIPAL DISPLAY PANEL

OXYGEN,
REFRIGERATED LIQUID
USP
UN1073
PRODUCED BY AIR LIQUEFACTION
Rx Only.